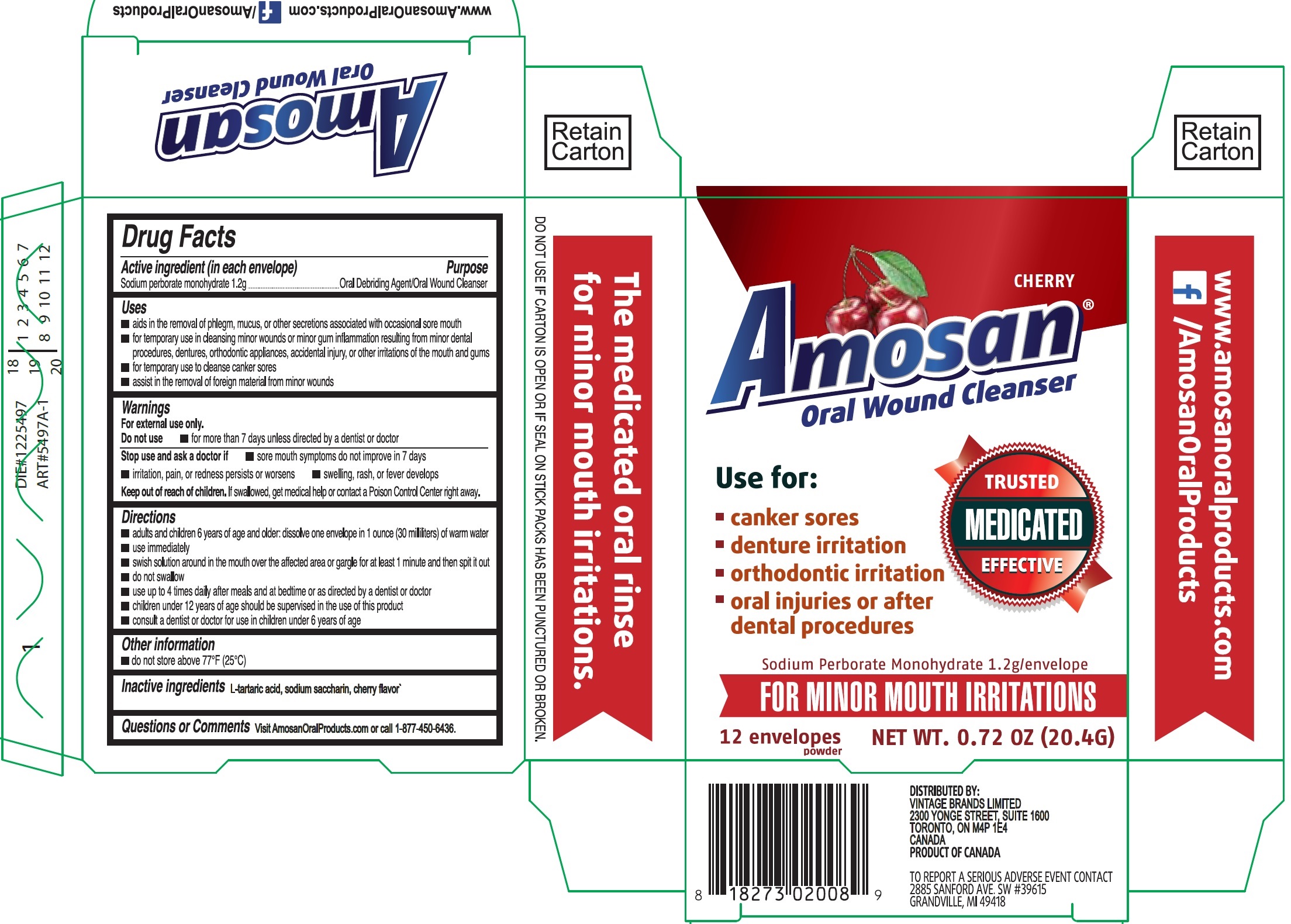 DRUG LABEL: Amosan Oral Wound Cleanser Cherry
NDC: 71223-002 | Form: POWDER, FOR SOLUTION
Manufacturer: Vintage Brands Limited
Category: otc | Type: HUMAN OTC DRUG LABEL
Date: 20241030

ACTIVE INGREDIENTS: SODIUM PERBORATE MONOHYDRATE 1.2 g/1.7 g
INACTIVE INGREDIENTS: TARTARIC ACID; SACCHARIN SODIUM

Amosan Oral Wound Cleanser

Active ingredient (in each envelope)

Sodium perborate monohydrate 1.2g

Purpose

Oral Debriding Agent/Oral Wound Cleanser

Uses

- aids in the removal of phlegm, mucus, or other secretions with occasional sore mouth
- for temporary use in cleansing minor wounds or minor gum inflammation resulting from minor dental procedures, dentures, orthodontic appliances, accidental injury,or other irritations of the mouth and gums
- for temporary use to cleanse canker sores
- assist in the removal of foreign material from minor wounds

Warnings

For external use only.

Do not use

- for more than 7 days unless directed by a dentist or doctor

Stop use and ask a doctor if

- sore mouth symptoms do not improve in 7 days
- irritation, pain, or redness persists or worsens
- swelling, rash, or faver develops

Keep out of reach of children.

If swallowed, get medical help or contact a Poison Control Center right away.

Directions

- adults and children 6 years of age and older: dissolve one envelope in 1 ounce (30 milliliters) of warm water
- use immediately
- swish solution around in the mouth over the affected area on gargle for at least 1 minute and then spit it out
- do not swallow
- use up to 4 times daily after meals and at bedtime or as directed by a dentist or doctor
- children under 12 years of age should be supervised in the use of this product
- consult a dentist or doctor for use in children under 6 years of age

Other information

do not store above 77°F (25°C)

Inactive ingredients

L-tartaric acid, sodium saccharin, cherry flavor'

Questions or Comments

Visit AmosanOralProducts.com or call 1-877-450-6436.